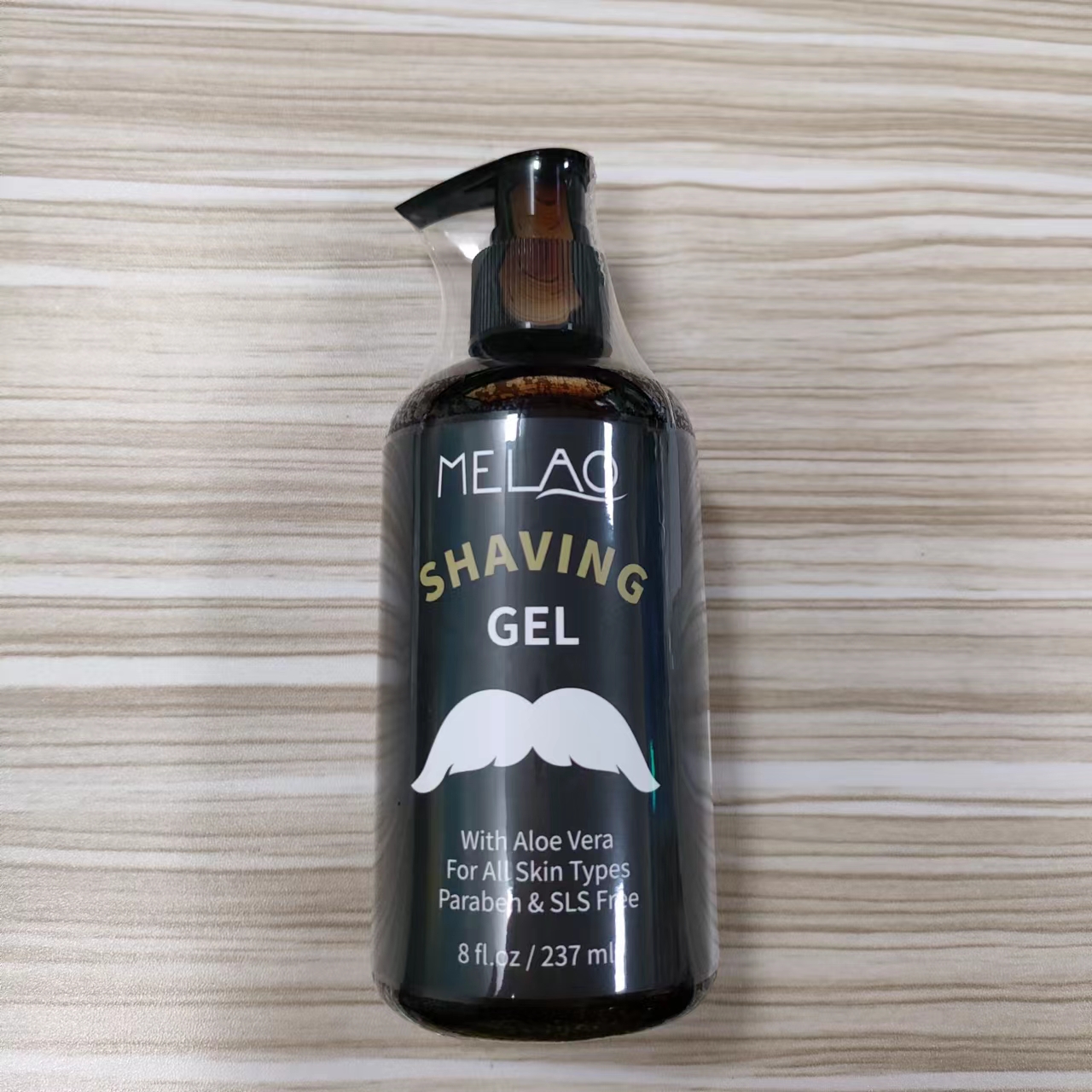 DRUG LABEL: MELAO Shaving Gel
NDC: 74458-137 | Form: GEL
Manufacturer: Guangzhou Yilong Cosmetics Co., Ltd
Category: otc | Type: HUMAN OTC DRUG LABEL
Date: 20241024

ACTIVE INGREDIENTS: ALOE BARBADENSIS LEAF JUICE 15 g/100 mL
INACTIVE INGREDIENTS: FRAGRANCE 13576; GLYCERIN; POLYSORBATE 20; AQUA; CARBOMER; PHENOXYETHANOL; TRIETHANOLAMINE

MELAO SHAVING GEL

ACTIVE INGREDIENT

Aloe Barbadensis Leaf Juice 15%

INACTIVE INGREDIENT

Aqua

Glycerin

Polysorbate 20

Triethanolamine

Carbomer

Phenoxyethanol

Fragrance

PURPOSE

Lubricates the shaving process and relieves burning or stinging sensation after shaving.

WARNINGS

For external use only.

Stop use and ask a doctor if rash occurs.

INDICATIONS AND USAGE

Dispense gel into hands then apply to wet face. Proceed to shave, rinsing blade between passes. Pat dry face with towel after shaving.

DOSAGE AND ADMINISTRATION

Dispense gel into hands then apply to wet face. Proceed to shave, rinsing blade between passes. Pat dry face with towel after shaving

Do not use on damaged or broken skin.

When using this product keep out of eyes. Rinse with water to remove.

Keep out of reach of children. If swallowed, get medical help or contact a Poison Control Center right away.